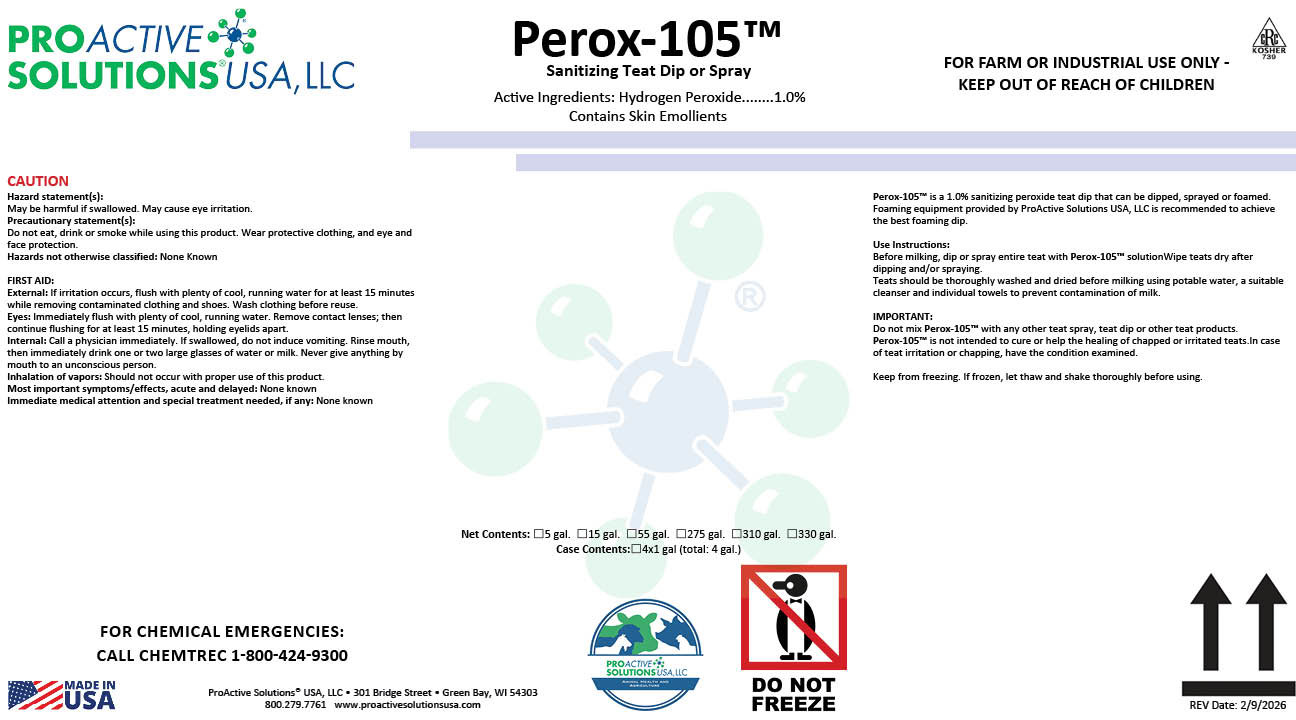 DRUG LABEL: Perox 105
NDC: 63927-4321 | Form: LIQUID
Manufacturer: ProActive Solutions USA, LLC
Category: animal | Type: OTC ANIMAL DRUG LABEL
Date: 20260210

ACTIVE INGREDIENTS: HYDROGEN PEROXIDE 1 kg/100 kg

Perox 105

Perox 105

Perox-105™ is a 1.0% sanitizing peroxide teat dip that can be dipped, sprayed or foamed.
Foaming equipment provided by ProActive Solutions USA, LLC is recommended to achieve
the best foaming dip.
Use Instructions:
Before milking, dip or spray entire teat with Perox-105™ solutionWipe teats dry after
dipping and/or spraying.
Teats should be thoroughly washed and dried before milking using potable water, a suitable
cleanser and individual towels to prevent contamination of milk.
IMPORTANT:
Do not mix Perox-105™ with any other teat spray, teat dip or other teat products.
Perox-105™ is not intended to cure or help the healing of chapped or irritated teats.In case
of teat irritation or chapping, have the condition examined.
Keep from freezing. If frozen, let thaw and shake thoroughly before using.

Hazard statement(s):
May be harmful if swallowed. May cause eye irritation.
Precautionary statement(s):
Do not eat, drink or smoke while using this product. Wear protective clothing, and eye and
face protection.
Hazards not otherwise classified: None Known
FIRST AID:
External: If irritation occurs, flush with plenty of cool, running water for at least 15 minutes
while removing contaminated clothing and shoes. Wash clothing before reuse.
Eyes: Immediately flush with plenty of cool, running water. Remove contact lenses; then
continue flushing for at least 15 minutes, holding eyelids apart.
Internal: Call a physician immediately. If swallowed, do not induce vomiting. Rinse mouth,
then immediately drink one or two large glasses of water or milk. Never give anything by
mouth to an unconscious person.
Inhalation of vapors: Should not occur with proper use of this product.
Most important symptoms/effects, acute and delayed: None known
Immediate medical attention and special treatment needed, if any: None known